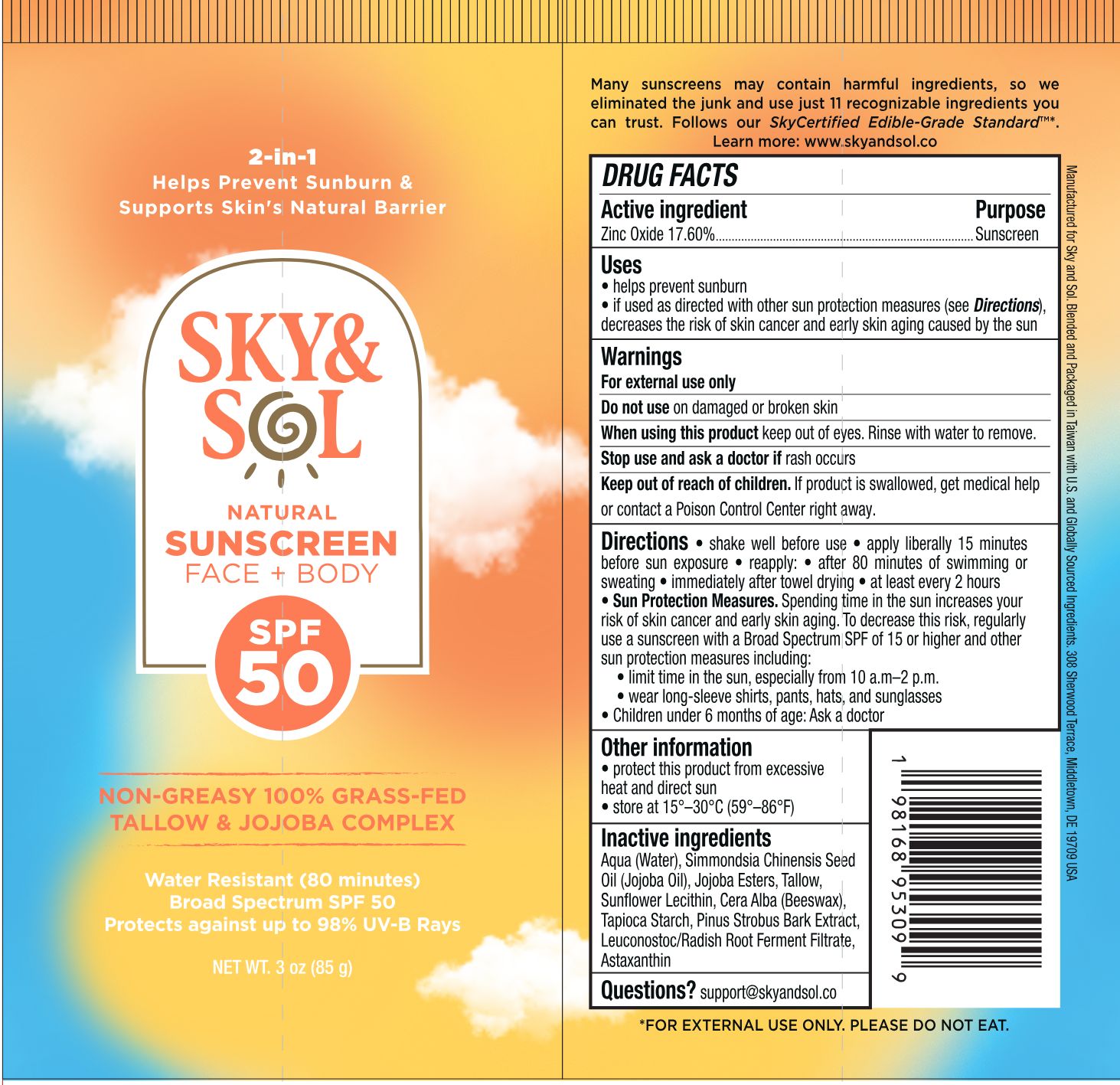 DRUG LABEL: Sky and Sol Face and Body Sunscreen Spf 50
NDC: 84632-3056 | Form: CREAM
Manufacturer: Delta Ecommerce LLC
Category: otc | Type: HUMAN OTC DRUG LABEL
Date: 20260201

ACTIVE INGREDIENTS: ZINC OXIDE 14.96 g/85 g
INACTIVE INGREDIENTS: TAPIOCA STARCH; ASTAXANTHIN; AQUA; LEUCONOSTOC/RADISH ROOT FERMENT FILTRATE; BEESWAX; PINUS STROBUS BARK; TALLOW; SIMMONDSIA CHINENSIS (JOJOBA) SEED OIL; HYDROLYZED JOJOBA ESTERS; LECITHIN, SUNFLOWER

PURPOSE

Sunscreen

INDICATIONS AND USAGE

helps prevent sunburn; if used as directed with other sun protection measures (see Directions), decreases the risk of skin cancer and early skin aging caused by the sun

WARNINGS

For external use only.
Do not use on damaged or broken skin.

When using this product, keep out of eyes. Rinse with water to remove.
Stop use and ask a doctor if rash occurs.

KEEP OUT OF REACH OF CHILDREN

Keep out of reach of childen. If swallowed, get medical help or contact a Poison Control Center right away.

INACTIVE INGREDIENT

AQUA
TALLOW
JOJOBA OIL
HYDROLYZED JOJOBA ESTERS
LECITHIN, SUNFLOWER
BEESWAX
TAPIOCA STARTCH
PINUS STROBUS BARK
ASTAXANTHIN
LEUCONOSTOC/RADISH ROOT FERMENT FILTRATE

DOSAGE AND ADMINISTRATION

Shake well before use.
Apply literally 15 minutes before sun exposure.
Reapply:
after 80 minutes of swimming or sweating
immediately after towel drying
at least every 2 hours